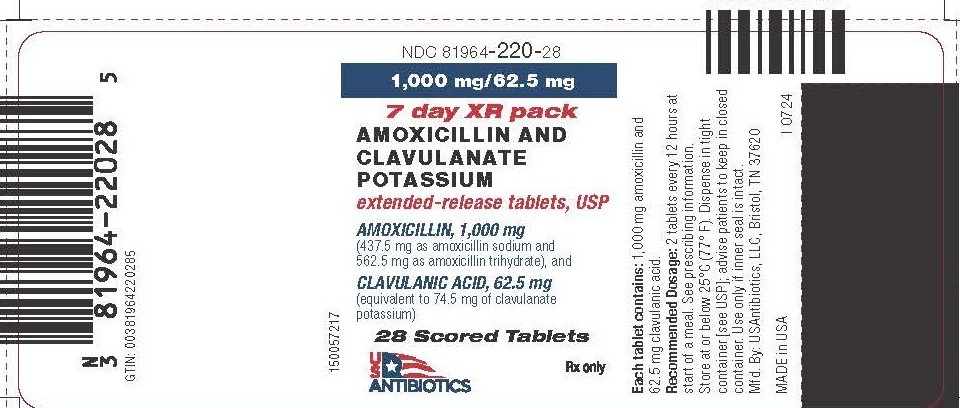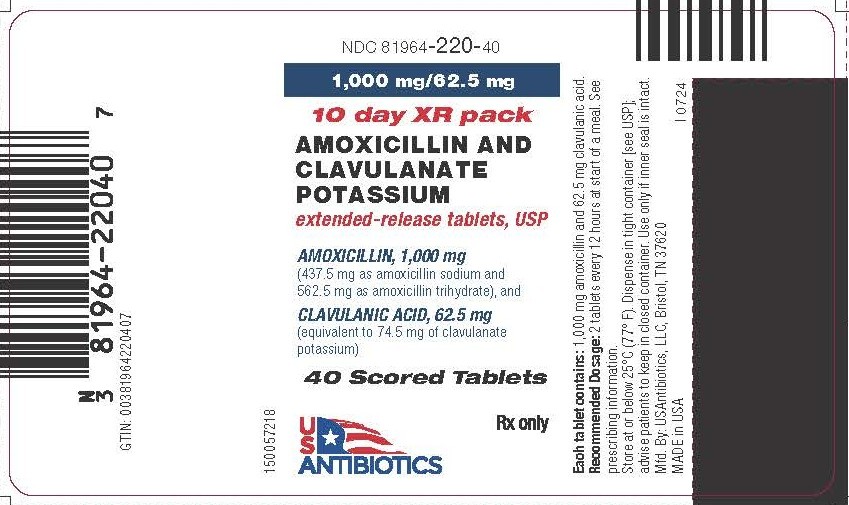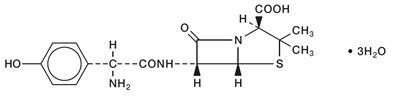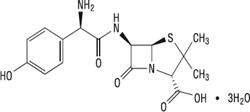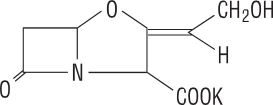 DRUG LABEL: Amoxicillin and Clavulanate Potassium
NDC: 81964-220 | Form: TABLET, FILM COATED, EXTENDED RELEASE
Manufacturer: USAntibiotics, LLC
Category: prescription | Type: HUMAN PRESCRIPTION DRUG LABEL
Date: 20251212

ACTIVE INGREDIENTS: AMOXICILLIN 562.5 mg/1 1; CLAVULANATE POTASSIUM 62.5 mg/1 1; AMOXICILLIN SODIUM 437.5 mg/1 1
INACTIVE INGREDIENTS: CITRIC ACID MONOHYDRATE; SILICON DIOXIDE; HYPROMELLOSES; MAGNESIUM STEARATE; MICROCRYSTALLINE CELLULOSE; POLYETHYLENE GLYCOL, UNSPECIFIED; SODIUM STARCH GLYCOLATE TYPE A POTATO; TITANIUM DIOXIDE; XANTHAN GUM

HIGHLIGHTS OF PRESCRIBING INFORMATION

These highlights do not include all the information needed to use Amoxicillin and Clavulanate Potassium Extended Release Tabletssafely and effectively. See full prescribing information for Amoxicillin and Clavulanate Potassium Extended Release Tablets.
Amoxicillin and Clavulanate Potassium Extended Release Tablets, for oral use.
Initial U.S. Approval: 2002

RECENT MAJOR CHANGES

Indications and Usage (1) | 12/2024
Dosage and Administration, Dosage in Pediatric Patients (2.3) | 12/2024
Warnings and Precautions, Drug-induced Enterocolitis Syndrome (DIES) (5.3) | 5/2024

1 INDICATIONS AND USAGE

Amoxicillin and Clavulanate Potassium Extended Release Tablets is a combination of amoxicillin, a penicillin-class antibacterial and clavulanate potassium, a beta-lactamase inhibitor, indicated for treatment of adults and pediatric patients weighing greater than or equal to 40 kg who are able to swallow tablets with

- community-acquired pneumonia or
- acute bacterial sinusitis

due to confirmed, or suspected beta-lactamase-producing pathogens (i.e., H. influenzae, M. catarrhalis, H. parainfluenzae, K. pneumoniae, or methicillin-susceptible S. aureus) and S. pneumoniaewith reduced susceptibility to penicillin (i.e., penicillin MICs equal to 2 mcg/mL). (1)

Limitations of Use

Amoxicillin and Clavulanate Potassium Extended Release Tablets is not indicated for the treatment of infections due to S. pneumoniae with penicillin MICs greater than or equal to 4 mcg/mL. Data are limited with regard to infections due to S. pneumoniae with penicillin MICs greater than or equal to 4 mcg/mL. (1)

Usage

To reduce the development of drug-resistant bacteria and maintain the effectiveness of Amoxicillin and Clavulanate Potassium Extended Release Tablets and other antibacterial drugs, Amoxicillin and Clavulanate Potassium Extended Release Tablets should be used only to treat or prevent infections that are proven or strongly suspected to be caused by bacteria .(1)

2 DOSAGE AND ADMINISTRATION

- Adults and Pediatric Patients weighing greater than or equal to 40 kg who are able to swallow tablets: The recommended dosage of Amoxicillin and Clavulanate Potassium Extended Release Tablets is 4,000 mg/250 mg daily in divided doses at the start of a meal according to the following table. (2)

Indication | Dose | Duration
Acute bacterial sinusitis | Two (1,000 mg/62.5 mg) tablets every 12 hours | 10 days
Community-acquired pneumonia | Two (1,000 mg/62.5 mg) tablets every 12 hours | 7 to 10 days

3 DOSAGE FORMS AND STRENGTHS

- Extended-release Tablets: 1,000 mg/62.5 mg. (3)

4 CONTRAINDICATIONS

- History of a serious hypersensitivity reaction (e.g., anaphylaxis or Stevens-Johnson syndrome) to AUGMENTIN or to other beta‑lactams (e.g., penicillins or cephalosporins). (4.1)
- History of cholestatic jaundice/hepatic dysfunction associated with AUGMENTIN. (4.2)
- In patients with severe renal impairment (creatinine clearance less than 30 mL/min) and in hemodialysis patients. (4.3)

5 WARNINGS AND PRECAUTIONS

- Serious (including fatal) hypersensitivity reactions: Discontinue Amoxicillin and Clavulanate Potassium Extended Release Tablets if a reaction occurs and institute appropriate therapy. (5.1)
- Severe cutaneous adverse reactions (SCAR): Monitor closely. Discontinue if rash progresses. (5.2)
- Drug-induced enterocolitis syndrome (DIES) has been reported with use of amoxicillin, a component of Amoxicillin and Clavulanate Potassium Extended Release Tablets. If this occurs, discontinue Amoxicillin and Clavulanate Potassium Extended Release Tablets and institute appropriate therapy. (5.3)
- Hepatic dysfunction and cholestatic jaundice: Discontinue if signs/symptoms of hepatitis occur. Monitor liver function tests in patients with hepatic impairment. (5.4)
- Clostridioides difficile-associated diarrhea (CDAD): Evaluate patients if diarrhea occurs. (5.5)
- Patients with mononucleosis who receive Amoxicillin and Clavulanate Potassium Extended Release Tablets develop skin rash. Avoid Amoxicillin and Clavulanate Potassium Extended Release Tablets use in these patients. (5.6)

6 ADVERSE REACTIONS

The most frequently reported adverse reactions were (incidence >2%) diarrhea, vaginal mycosis, nausea, and loose stools. (6.1)

To report SUSPECTED ADVERSE REACTIONS, contact USAntibiotics, LLC at 1-844-454-5532 or FDA at 1-800-FDA-1088 or www.fda.gov/medwatch.

7 DRUG INTERACTIONS

- Co-administration with probenecid is not recommended. (7.1)
- Concomitant use Amoxicillin and Clavulanate Potassium Extended Release Tablets and oral anticoagulants may increase the prolongation of prothrombin time. (7.2)
- Co-administration with allopurinol increases the risk of rash. (7.3)
- Amoxicillin and Clavulanate Potassium Extended Release Tablets may reduce efficacy of oral contraceptives. (7.4)

8 USE IN SPECIFIC POPULATIONS

Renal Impairment:Amoxicillin and Clavulanate Potassium Extended Release Tablets has not been studied in patients with renal impairment. (8.6)

FULL PRESCRIBING INFORMATION

1 INDICATIONS AND USAGE

Amoxicillin and Clavulanate Potassium Extended Release Tablets is indicated for the treatment of infections in adults and pediatric patients weighing greater than or equal to 40 kg who are able to swallow tablets with:

- community-acquired pneumonia or
- acute bacterial sinusitis

due to confirmed, or suspected beta-lactamase-producing pathogens (i.e., H. influenzae, M. catarrhalis, H. parainfluenzae, K. pneumoniae, or methicillin-susceptible S. aureus) and S. pneumoniae with reduced susceptibility to penicillin (i.e., penicillin MICs equal to 2 mcg/mL).

Limitations of Use

Amoxicillin and Clavulanate Potassium Extended Release Tablets is not indicated for the treatment of infections due to S. pneumoniae with penicillin MICs greater than or equal to 4 mcg/mL. Data are limited with regard to infections due to S. pneumoniae with penicillin MICs greater than or equal to 4 mcg/ mL [see Clinical Studies (14)].

Usage

To reduce the development of drug-resistant bacteria and maintain the effectiveness of Amoxicillin and Clavulanate Potassium Extended Release Tablets and other antibacterial drugs, Amoxicillin and Clavulanate Potassium Extended Release Tablets should be used only to treat or prevent infections that are proven or strongly suspected to be caused by susceptible bacteria. When culture and susceptibility information are available, they should be considered in selecting or modifying antibacterial therapy. In the absence of such data, local epidemiology and susceptibility patterns may contribute to the empiric selection of therapy.

In patients with community-acquired pneumonia in whom penicillin-resistant S. pneumoniae is suspected, bacteriological studies should be performed to determine the causative organisms and their susceptibility when Amoxicillin and Clavulanate Potassium Extended Release Tablets is prescribed.

Acute bacterial sinusitis or community-acquired pneumonia due to a penicillin-susceptible strain of S. pneumoniae plus a beta-lactamase-producing pathogen can be treated with another amoxicillin and clavulanate potassium product containing lower daily doses of amoxicillin (i.e., 500 mg every 8 hours or 875 mg every 12 hours). Acute bacterial sinusitis or community-acquired pneumonia due to S. pneumoniae alone can be treated with amoxicillin.

2 DOSAGE AND ADMINISTRATION

2.1 Important Administration Instructions

Amoxicillin and Clavulanate Potassium Extended Release Tablets should be taken at the start of a meal to enhance the absorption of amoxicillin and to minimize the potential for gastrointestinal intolerance. Amoxicillin and Clavulanate Potassium Extended Release Tablets is not recommended to be taken with a high-fat meal because clavulanate absorption is decreased [see Clinical Pharmacology (12.3)].

2.2 Dosage in Adults Patients

The recommended dosage of Amoxicillin and Clavulanate Potassium Extended Release Tablets is 4,000 mg/250 mg daily in divided doses according to the following table:

Table 1: Recommended Dosage of Amoxicillin and Clavulanate Potassium Extended Release Tablets in Adult Patients
Indication | Dose | Duration
Acute bacterial sinusitis | Two (1,000 mg/62.5 mg) tablets every 12 hours | 10 days
Community-acquired pneumonia | Two (1,000 mg/62.5 mg) tablets every 12 hours | 7 to 10 days

Amoxicillin and Clavulanate Potassium Extended Release Tablets can be split in half along the score line for patients with difficulty swallowing the tablets whole. Both halves of the tablet must be taken immediately.

2.3 Dosage in Pediatric Patients

Pediatric patients who weigh 40 kg or more and can swallow tablets should receive the adult dose [see Dosage and Administration (2.2) and Use in Specific Populations (8.4)].

2.4 Dosage in Patients with Hepatic Impairment

Hepatically impaired patients should be dosed with caution and hepatic function monitored at regular intervals [see Warnings and Precautions (5.4)].

2.5 Switching Between Dosage Forms and Strengths

Amoxicillin and Clavulanate Potassium Extended Release Tablets is NOT substitutable on a mg-to-mg basis with other formulations of Amoxicillin and Clavulanate. In addition, the extended-release tablets provide an extended time course of plasma amoxicillin concentrations compared to immediate-release tablets. Thus, two Amoxicillin and Clavulanate 500 mg tablets are not equivalent to one Amoxicillin and Clavulanate Potassium Extended Release Tablets 1,000 mg tablet.

3 DOSAGE FORMS AND STRENGTHS

- Amoxicillin and Clavulanate Potassium Extended Release Tablets; 1,000 mg/62.5 mg:

Each white, oval film-coated bilayer scored tablet, debossed with "AUGMENTIN XR", contains 1,000 mg of amoxicillin (as amoxicillin sodium and amoxicillin trihydrate) and 62.5 mg clavulanic acid as the potassium salt.

4 CONTRAINDICATIONS

4.1 Serious Hypersensitivity Reactions

Amoxicillin and Clavulanate Potassium Extended Release Tablets is contraindicated in patients with a history of serious hypersensitivity reactions (e.g., anaphylaxis or Stevens-Johnson syndrome) to amoxicillin, clavulanate or to other beta-lactam antibacterial drugs (e.g., penicillins and cephalosporins).

4.2 Cholestatic Jaundice/Hepatic Dysfunction

Amoxicillin and Clavulanate Potassium Extended Release Tablets is contraindicated in patients with a previous history of cholestatic jaundice/hepatic dysfunction associated with treatment with amoxicillin/clavulanate potassium.

4.3 Renal Impairment

Amoxicillin and Clavulanate Potassium Extended Release Tablets is contraindicated in patients with severe renal impairment (creatinine clearance less than 30 mL/min) and in hemodialysis patients.

5 WARNINGS AND PRECAUTIONS

5.1 Serious Allergic Reactions, including Anaphylaxis

Serious and occasionally fatal hypersensitivity (anaphylactic) reactions have been reported in patients receiving Amoxicillin and Clavulanate Potassium Extended Release Tablets. These reactions are more likely to occur in individuals with a history of penicillin hypersensitivity and/or a history of sensitivity to multiple allergens. Before initiating therapy with Amoxicillin and Clavulanate Potassium Extended Release Tablets, careful inquiry should be made regarding previous hypersensitivity reactions to penicillins, cephalosporins, or other allergens. If an allergic reaction occurs, discontinue Amoxicillin and Clavulanate Potassium Extended Release Tablets and institute appropriate therapy.

5.2 Severe Cutaneous Adverse Reactions

Amoxicillin and Clavulanate Potassium Extended Release Tablets may cause severe cutaneous adverse reactions (SCAR), such as Stevens-Johnson syndrome (SJS), toxic epidermal necrolysis (TEN), drug reaction with eosinophilia and systemic symptoms (DRESS), and acute generalized exanthematous pustulosis (AGEP). If patients develop a skin rash, they should be monitored closely, and Amoxicillin and Clavulanate Potassium Extended Release Tablets discontinued if lesions progress.

5.3 Drug-Induced Enterocolitis Syndrome

Drug-induced enterocolitis syndrome (DIES) has been reported with use of amoxicillin, a component of Amoxicillin and Clavulanate Potassium Extended Release Tablets [see Adverse Reactions (6.2)] , with most cases occurring in pediatric patients </=18 years of age. DIES is a non-IgE mediated hypersensitivity reaction characterized by protracted vomiting occurring 1 to 4 hours after drug ingestion in the absence of skin or respiratory symptoms. DIES may be associated with pallor, lethargy, hypotension, shock, diarrhea within 24 hours after ingesting amoxicillin, and leukocytosis with neutrophilia. If DIES occurs, discontinue Amoxicillin and Clavulanate Potassium Extended Release Tablets and institute appropriate therapy.

5.4 Hepatic Dysfunction

Use Amoxicillin and Clavulanate Potassium Extended Release Tablets with caution in patients with evidence of hepatic dysfunction. Hepatic toxicity associated with the use of Amoxicillin and Clavulanate Potassium is usually reversible. Deaths have been reported (fewer than one death reported per estimated four million prescriptions worldwide). These have generally been cases associated with serious underlying diseases or concomitant medications [see Contraindications (4.2), and Adverse Reactions (6.2)].

5.5 Clostridioides difficile-Associated Diarrhea (CDAD)

Clostridioides difficile-associated diarrhea (CDAD) has been reported with use of nearly all antibacterial agents, including Amoxicillin and Clavulanate Potassium Extended Release Tablets, and may range in severity from mild diarrhea to fatal colitis. Treatment with antibacterial agents alters the normal flora of the colon leading to overgrowth of C. difficile.

C. difficile produces toxins A and B which contribute to the development of CDAD. Hypertoxin-producing strains of C. difficile

cause increased morbidity and mortality, as these infections can be refractory to antimicrobial therapy and may require colectomy. CDAD must be considered in all patients who present with diarrhea following antibacterial drug use. Careful medical history is necessary since CDAD has been reported to occur over two months after the administration of antibacterial agents.

If CDAD is suspected or confirmed, ongoing antibacterial drug use not directed against C. difficile may need to be discontinued. Appropriate fluid and electrolyte management, protein supplementation, antibacterial treatment of C. difficile, and surgical evaluation should be instituted as clinically indicated.

5.6 Skin Rash in Patients with Mononucleosis

A high percentage of patients with mononucleosis who receive amoxicillin develop an erythematous skin rash. Avoid Amoxicillin and Clavulanate Potassium Extended Release Tablets use in patients with mononucleosis.

5.7 Potential for Microbial Overgrowth

The possibility of superinfections with mycotic or bacterial pathogens should be considered during therapy. If superinfections occur (commonly involving Pseudomonas spp. or Candida spp.), the drug should be discontinued and/or appropriate therapy instituted.

5.8 Development of Drug-Resistant Bacteria

Prescribing Amoxicillin and Clavulanate Potassium Extended Release Tablets in the absence of a proven or strongly suspected bacterial infection or a prophylactic indication is unlikely to provide benefit to the patient and increases the risk of the development of drug-resistant bacteria.

6 ADVERSE REACTIONS

The following clinically significant adverse reactions are described elsewhere in the labeling:

- Anaphylactic reactions [see Warnings and Precautions (5.1)]
- Severe Cutaneous Adverse Reactions [see Warnings and Precautions (5.2)]
- Drug-Induced Enterocolitis Syndrome (DIES) [see Warnings and Precautions (5.3)]
- Hepatic Dysfunction [see Warnings and Precautions (5.4)]
- Clostridioides difficile-associated diarrhea (CDAD) [see Warnings and Precautions (5.5)]
- Skin Rash in Patients with Mononucleosis [see Warnings and Precautions (5.6)]

6.1 Clinical Trials Experience

Because clinical trials are conducted under widely varying conditions, adverse reaction rates observed in the clinical trials of a drug cannot be directly compared to rates in the clinical trials of another drug and may not reflect the rates observed in practice.

In clinical trials, 5,643 patients have been treated with Amoxicillin and Clavulanate Potassium Extended Release Tablets. The most frequently reported adverse reactions were diarrhea (15%), vaginal mycosis (3%), nausea (2%), and loose stools (2%). Amoxicillin and Clavulanate Potassium Extended Release Tablets had a higher rate of diarrhea which required corrective therapy (4% versus 3% for Amoxicillin and Clavulanate Potassium Extended Release Tablets and all comparators, respectively). Two percent of patients discontinued therapy due to adverse reactions.

6.2 Postmarketing Experience

The following adverse reactions have been identified during postmarketing use of Amoxicillin and Clavulanate products, including Amoxicillin and Clavulanate Potassium Extended Release Tablets. Because these reactions are reported voluntarily from a population of uncertain size, it is not always possible to reliably estimate their frequency or establish a causal relationship to drug exposure.

Gastrointestinal: Drug-induced enterocolitis syndrome (DIES), diarrhea, nausea, vomiting, indigestion, gastritis, stomatitis, glossitis, black “hairy” tongue, mucocutaneous candidiasis, enterocolitis, and hemorrhagic/pseudomembranous colitis. Onset of pseudomembranous colitis symptoms may occur during or after antibacterial treatment [see Warnings and Precautions (5.3, 5.5)] .

Immune: Hypersensitivity reactions, anaphylactic/anaphylactoid reactions (including shock), angioedema, serum sickness-like reactions (urticaria or skin rash accompanied by arthritis, arthralgia, myalgia, and frequently fever), hypersensitivity vasculitis [see Warnings and Precautions (5.1)] .

Skin and Appendages: Rashes, pruritus, urticaria, erythema multiforme, SJS, TEN, DRESS, AGEP, exfoliative dermatitis, and linear IgA bullous dermatosis [see Warnings and Precautions (5.1, 5.2, 5.6)] .

Liver: A moderate rise in AST (SGOT) and/or ALT (SGPT) has been noted in patients treated with ampicillin-class antibacterials, but the significance of these findings is unknown. Hepatic dysfunction, including hepatitis and cholestatic jaundice, [see Contraindications (4.2)], increases in serum transaminases (AST and/or ALT), serum bilirubin, and/or alkaline phosphatase, has been reported with Amoxicillin and Clavulanate. It has been reported more commonly in the elderly, in males, or in patients on prolonged treatment. The histologic findings on liver biopsy have consisted of predominantly cholestatic, hepatocellular, or mixed cholestatic-hepatocellular changes. The onset of signs/symptoms of hepatic dysfunction may occur during or several weeks after therapy has been discontinued. The hepatic dysfunction, which may be severe, is usually reversible. Deaths have been reported [see Contraindications (4.2), Warnings and Precautions (5.4)] .

Renal: Interstitial nephritis, hematuria, and crystalluria have been reported [see Overdosage (10)] .

Hemic and Lymphatic Systems: Anemia, including hemolytic anemia, thrombocytopenia, thrombocytopenic purpura, eosinophilia, leukopenia, and agranulocytosis have been reported during therapy with penicillins. These reactions are usually reversible on discontinuation of therapy and are believed to be hypersensitivity phenomena. There have been reports of increased prothrombin time in patients receiving Amoxicillin and Clavulanate and anticoagulant therapy concomitantly [see Drug Interactions (7.2)] .

Central Nervous System: Agitation, anxiety, behavioral changes, aseptic meningitis, confusion, convulsions, dizziness, headache, insomnia, and reversible hyperactivity have been reported.

Miscellaneous: Tooth discoloration (brown, yellow, or gray staining) has been reported. Most reports occurred in pediatric patients. Discoloration was reduced or eliminated with brushing or dental cleaning in most cases.

7 DRUG INTERACTIONS

7.1 Probenecid

Probenecid decreases the renal tubular secretion of amoxicillin. Concurrent use with Amoxicillin and Clavulanate Potassium Extended Release Tablets may result in increased and prolonged blood levels of amoxicillin. Co-administration of probenecid is not recommended.

7.2 Oral Anticoagulants

Abnormal prolongation of prothrombin time (increased international normalized ratio [INR]) has been reported in patients receiving amoxicillin and oral anticoagulants. Appropriate monitoring should be undertaken when anticoagulants are prescribed concurrently. Adjustments in the dose of oral anticoagulants may be necessary to maintain the desired level of anticoagulation.

7.3 Allopurinol

The concurrent administration of allopurinol and amoxicillin substantially increases the incidence of rashes in patients receiving both drugs as compared to patients receiving amoxicillin alone. It is not known whether this potentiation of amoxicillin rashes is due to allopurinol or the hyperuricemia present in these patients. In controlled clinical trials of Amoxicillin and Clavulanate Potassium Extended Release Tablets, 25 patients received concomitant allopurinol and Amoxicillin and Clavulanate Potassium Extended Release Tablets. No rashes were reported in these patients. However, this sample size is too small to allow for any conclusions to be drawn regarding the risk of rashes with concomitant Amoxicillin and Clavulanate Potassium Extended Release Tablets and allopurinol use.

7.4 Oral Contraceptives

Amoxicillin and Clavulanate Potassium Extended Release Tablets may affect intestinal flora, leading to lower estrogen reabsorption and reduced efficacy of combined oral estrogen/progesterone contraceptives.

7.5 Effects on Laboratory Tests

High urine concentrations of amoxicillin may result in false-positive reactions when testing for the presence of glucose in urine using CLINITEST®, Benedict’s Solution, or Fehling’s Solution. Since this effect may also occur with Amoxicillin and Clavulanate Potassium Extended Release Tablets, it is recommended that glucose tests based on enzymatic glucose oxidase reactions be used. Following administration of amoxicillin to pregnant women, a transient decrease in plasma concentration of total conjugated estriol, estriol-glucuronide, conjugated estrone, and estradiol has been noted.

8 USE IN SPECIFIC POPULATIONS

8.1 Pregnancy

Risk Summary

Available data from published epidemiologic studies and pharmacovigilance case reports over several decades of use with amoxicillin and clavulanate during pregnancy have not established a drug-associated risk of major birth defects, miscarriage, or adverse maternal outcomes. A study in women with preterm prelabor rupture of membranes (PPROM) reported that prophylactic treatment with amoxicillin and clavulanate may be associated with an increased risk of necrotizing enterocolitis in neonates (see Data). Reproduction studies performed in pregnant rodents, given oral doses up to approximately 1.6 times the amount of amoxicillin and 13 times the amount of clavulanate in the Maximum Human Recommended Dose (MHRD) of Amoxicillin and Clavulanate Potassium Extended Release Tablets, revealed no evidence of harm to the fetus (see Data).

The background risk of major birth defects and miscarriage for the indicated populations is unknown. All pregnancies have a background risk of birth defect, loss, or other adverse outcomes. In the U.S. general population, the estimated background risk of major birth defects and miscarriage in clinically recognized pregnancies is 2 to 4% and 15 to 20%, respectively.

Data

Human Data

One randomized, controlled trial included 4,826 pregnant women with premature rupture of fetal membranes who were randomly assigned to 250 mg erythromycin (n=1,197), 250 mg amoxicillin and 125 mg clavulanic acid (amoxicillin and clavulanate, n=1,212), amoxicillin and clavulanate and erythromycin (n=1,192), or placebo (n=1,225) four times daily for 10 days or until delivery. Amoxicillin and clavulanate was associated with a significantly increased rate of proven neonatal necrotizing enterocolitis: 1.9% (n = 24) in the amoxicillin and clavulanate only group versus 0.5% (n = 6) in the placebo group (p = 0.001), and 1.8% (n = 44) in the any amoxicillin and clavulanate group versus 0.7% (n =17) in the no amoxicillin and clavulanate group (p = 0.0005).

Animal Data

Reproduction studies performed in pregnant rats and mice given amoxicillin and clavulanate (2:1 ratio formulation) at oral doses up to 1,200 mg/kg/day revealed no evidence of harm to the fetus due to amoxicillin and clavulanate. In terms of body surface area, the doses in rats were 1.6 times the Maximum Human Recommended Dose (MHRD) of amoxicillin and 13 times the MHRD for clavulanate in Amoxicillin and Clavulanate Potassium Extended Release Tablets. For mice, these doses were 0.9 and 7.4 times the MHRD of amoxicillin and clavulanate, respectively.

8.2 Lactation

Risk Summary

Data from a published clinical lactation study report that amoxicillin is present in human milk . There are reports of diarrhea, irritability, and rash in infants exposed to amoxicillin and clavulanate through breast milk; therefore, infants exposed to Amoxicillin and Clavulanate Potassium Extended Release Tablets should be monitored for these symptoms. There are no data on the effects of amoxicillin and clavulanate on milk production. The developmental and health benefits of breastfeeding should be considered along with the mother’s clinical need for Amoxicillin and Clavulanate Potassium Extended Release Tablets and any potential adverse effects on the breastfed child from Amoxicillin and Clavulanate Potassium Extended Release Tablets or from the underlying maternal condition.

8.4 Pediatric Use

The safety and effectiveness of Amoxicillin and Clavulanate Potassium Extended Release Tablets have been established for pediatric patients weighing greater than or equal to 40 kg who are able to swallow tablets. Use of Amoxicillin and Clavulanate Potassium Extended Release Tablets in these pediatric patients is supported by evidence from adequate and well-controlled trials of adults with acute bacterial sinusitis and community-acquired pneumonia with additional data from a pediatric pharmacokinetic study.

A pharmacokinetic study in pediatric patients (7 to 15 years of age and weighing greater than or equal to 40 kg) was conducted [see Clinical Pharmacology (12.3)]. The adverse event profile in 44 pediatric patients who received at least one dose of Amoxicillin and Clavulanate Potassium Extended Release Tablets was consistent with the established adverse event profile for the product in adults.

8.5 Geriatric Use

Of the total number of subjects in clinical studies of Amoxicillin and Clavulanate Potassium Extended Release Tablets, 18% were 65 years or older and 7% were 75 years or older. No overall differences in safety and effectiveness were observed between these subjects and younger subjects, and other clinical experience has not reported differences in responses between the elderly and younger patients, but a greater sensitivity of some older individuals cannot be ruled out.

Amoxicillin and Clavulanate Potassium Extended Release Tablets is known to be substantially excreted by the kidney, and the risk of dose dependent toxic reactions to this drug may be greater in patients with impaired renal function. Because elderly patients are more likely to have decreased renal function, it may be useful to monitor renal function.

8.6 Renal Impairment

The pharmacokinetics of Amoxicillin and Clavulanate Potassium Extended Release Tablets have not been studied in patients with renal impairment. Amoxicillin and Clavulanate Potassium Extended Release Tablets is contraindicated in patients with a creatinine clearance of less than 30 mL/min and in hemodialysis patients [see Contraindications (4.3)].

8.7 Hepatic Impairment

Hepatically impaired patients should be dosed with caution and hepatic function monitored at regular intervals [see Contraindications (4.2), Warnings and Precautions (5.4)] .

10 OVERDOSAGE

Following overdosage, patients have experienced primarily gastrointestinal symptoms including stomach and abdominal pain, vomiting, and diarrhea. Rash, hyperactivity, or drowsiness have also been observed in a small number of patients.

In the case of overdosage, discontinue Amoxicillin and Clavulanate Potassium Extended Release Tablets, treat symptomatically, and institute supportive measures as required. If the overdosage is very recent and there is no contraindication, an attempt at emesis or other means of removal of drug from the stomach may be performed. A prospective study of 51 pediatric patients at a poison control center suggested that overdosages of less than 250 mg/kg of amoxicillin are not associated with significant clinical symptoms and do not require gastric emptying.^1

Interstitial nephritis resulting in oliguric renal failure has been reported in a small number of patients after overdosage with amoxicillin.

Crystalluria, in some cases leading to renal failure, has also been reported after amoxicillin overdosage in adult and pediatric patients. In the case of overdosage, adequate fluid intake and diuresis should be maintained to reduce the risk of amoxicillin crystalluria.

Renal impairment appears to be reversible with cessation of drug administration. High blood levels may occur more readily in patients with impaired renal function because of decreased renal clearance of both amoxicillin and clavulanate. Both amoxicillin and clavulanate are removed from the circulation by hemodialysis.

11 DESCRIPTION

Amoxicillin and Clavulanate Potassium Extended Release Tablets is an oral antibacterial combination consisting of the semisynthetic antibacterial amoxicillin (present as amoxicillin sodium and amoxicillin trihydrate) and the beta-lactamase inhibitor clavulanate potassium (the potassium salt of clavulanic acid). Amoxicillin is an analog of ampicillin, derived from the basic penicillin nucleus, 6-aminopenicillanic acid. The amoxicillin trihydrate molecular formula is C16H19N3O5S•3H2O, and the molecular weight is 419.45.

Chemically, amoxicillin trihydrate is (2S,5R,6R)-6-[(R)-(-)-2-Amino-2-(p-hydroxyphenyl)acetamido]-3,3-dimethyl-7-oxo-4-thia-1-azabicyclo[3.2.0]heptane-2-carboxylic acid trihydrate and may be represented structurally as:

The amoxicillin sodium molecular formula is C16H18N3NaO5S, and the molecular weight is 387.39. Chemically, amoxicillin sodium is [2 -[2α,5α,6β(S*)]]-6-[[Amino (4-hydroxyphenyl)acetyl]amino]-3,3-dimethyl-7-oxo-4-thia-1-azabicyclo[3.2.0]heptane-2-carboxylic acid monosodium salt and may be represented structurally as:

Clavulanic acid is produced by the fermentation of Streptomyces clavuligerus. It is a beta-lactam structurally related to the penicillins and possesses the ability to inactivate a wide variety of beta-lactamases by blocking the active sites of these enzymes. Clavulanic acid is particularly active against the clinically important plasmid-mediated beta-lactamases frequently responsible for transferred drug resistance to penicillins and cephalosporins. The clavulanate potassium molecular formula is C8H8KNO5, and the molecular weight is 237.25.

Chemically, clavulanate potassium is potassium (Z)-(2R,5R)-3-(2-hydroxyethylidene)-7-oxo-4-oxa-1-azabicyclo[3.2.0]-heptane-2-carboxylate, and may be represented structurally as:

Each tablet of Amoxicillin and Clavulanate Potassium Extended Release Tablets contains 1,000 mg of amoxicillin (437.5 mg of amoxicillin equivalent to 463.8 mg of amoxicillin sodium and 562.5 mg of amoxicillin in the form of amoxicillin trihydrate), and 62.5 mg of clavulanic acid (equivalent to 74.5 mg of clavulanate potassium).

Inactive Ingredients: Citric acid, colloidal silicon dioxide, hypromellose, magnesium stearate, microcrystalline cellulose, polyethylene glycol, sodium starch glycolate, titanium dioxide, and xanthan gum.

Each tablet of Amoxicillin and Clavulanate Potassium Extended Release Tablets contains approximately 13 mg of potassium and 30 mg of sodium.

12 CLINICAL PHARMACOLOGY

12.1 Mechanism of Action

Amoxicillin and Clavulanate Potassium Extended Release Tablets is an antibacterial drug [see Clinical Pharmacology (12.4)] .

12.3 Pharmacokinetics

Amoxicillin and Clavulanate Potassium Extended Release Tablets is an extended-release formulation which provides sustained plasma concentrations of amoxicillin. Amoxicillin systemic exposure achieved with Amoxicillin and Clavulanate Potassium Extended Release Tablets is similar to that produced by the oral administration of equivalent doses of amoxicillin alone.

Absorption

Amoxicillin and clavulanate potassium are well absorbed from the gastrointestinal tract after oral administration of Amoxicillin and Clavulanate Potassium Extended Release Tablets.

In a study of healthy adult volunteers, the pharmacokinetics of Amoxicillin and Clavulanate Potassium Extended Release Tablets were compared when administered in a fasted state, at the start of a standardized meal (612 kcal, 89.3 g carb, 24.9 g fat, and 14 g protein), or 30 minutes after a high‑fat meal.

When the systemic exposure to both amoxicillin and clavulanate is taken into consideration, Amoxicillin and Clavulanate Potassium Extended Release Tablets is optimally administered at the start of a standardized meal. Absorption of amoxicillin is decreased in the fasted state. Amoxicillin and Clavulanate Potassium Extended Release Tablets is not recommended to be taken with a high‑fat meal, because clavulanate absorption is decreased. The pharmacokinetics of the components of Amoxicillin and Clavulanate Potassium Extended Release Tablets following administration of two Amoxicillin and Clavulanate Potassium Extended Release Tablets tablets at the start of a standardized meal are presented in Table 2.

Table 2: Mean (SD) Pharmacokinetic Parmameters for Amoxicillin and Clavulanate Following Oral Administration of Two Amoxicillin and Clavulanate Potassium Extended Release Tablets (2,000 mg/125 mg) to Healthy Adult Volunteers (n=55) Fed a Standardized Meal
Parameter (units) | Amoxicillin | Clavulanate
AUC(0‑inf)(mcg•hr/mL) | 71.6 (16.5) | 5.29 (1.55)
Cmax(mcg/mL) | 17.0 (4.0) | 2.05 (0.80)
Tmax(hours)a | 1.50 (1.00 to 6.00) | 1.03 (0.75 to 3.00)
T1/2(hours) | 1.27 (0.20) | 1.03 (0.17)

aMedian (range)

The half-life of amoxicillin after the oral administration of Amoxicillin and Clavulanate Potassium Extended Release Tablets is approximately 1.3 hours, and that of clavulanate is approximately 1.0 hour.

Distribution

Neither component in Amoxicillin and Clavulanate Potassium Extended Release Tablets is highly protein‑bound; clavulanate has been found to be approximately 25% bound to human serum and amoxicillin approximately 18% bound.

Amoxicillin diffuses readily into most body tissues and fluids, with the exception of the brain and spinal fluid. The results of experiments involving the administration of clavulanic acid to animals suggest that this compound, like amoxicillin, is well distributed in body tissues.

Excretion

Clearance of amoxicillin is predominantly renal, with approximately 60% to 80% of the dose being excreted unchanged in urine, whereas clearance of clavulanate has both a renal (30% to 50%) and a non‑renal component.

Specific Populations

Pediatric Patients

In a study of pediatric patients with acute bacterial sinusitis, 7 to 15 years of age, and weighing at least 40 kg, the pharmacokinetics of amoxicillin and clavulanate were assessed following administration of Amoxicillin and Clavulanate Potassium Extended Release Tablets 2,000 mg/125 mg (as two 1,000 mg/62.5 mg tablets) every 12 hours with food (Table 3).

Table 3: Mean (SD) Pharmacokinetic Parameters for Amoxicillin and Clavulanate Following Oral Administration of Two Amoxicillin and Clavulanate Extended Release Tablets (2,000 mg/125 mg) Every 12 Hours with Food in Pediatric Patients (7 to 15 Years of Age and Weighing greater than or equal to 40 kg) With Acute Bacterial Sinusitis
Parameter (units) | Amoxicillin (n = 24) | Clavulanate (n = 23)
AUC (0-t)(mcg•hr/mL) | 57.8 (15.6) | 3.18 (1.37)
Cmax(mcg/mL) | 11.0 (3.34) | 1.17 (0.67)
Tmax (hours)a | 2.0 (1.0 to 5.0) | 1.1 (1.0 to 4.0)
T½(hours) | 3.32 (2.21)b | 0.94 (0.13)c

a Median (range).

b n equals 18.

c n equals 17.

Drug Interaction Studies
Clinical Studies
Concurrent administration of probenecid delays amoxicillin excretion but does not delay renal excretion of clavulanate [see Drug Interactions (7.1)] .

In a study of adults, the pharmacokinetics of amoxicillin and clavulanate were not affected by administration of an antacid (MAALOX®), either simultaneously with or 2 hours after Amoxicillin and Clavulanate Potassium Extended Release Tablets.

12.4 Clinical Pharmacology

Mechanism of Action
Amoxicillin binds to penicillin-binding proteins within the bacterial cell wall and inhibits bacterial cell wall synthesis.

Clavulanic acid is a beta-lactam, structurally related to penicillin, that may inactivate certain beta‑lactamase enzymes.

Resistance
Resistance to penicillins may be mediated by destruction of the beta-lactam ring by a beta-lactamase, altered affinity of penicillin for target, or decreased penetration of the antibacterial drug to reach the target site. Amoxicillin alone is susceptible to degradation by beta‑lactamases, and therefore its spectrum of activity does not include bacteria that produce these enzymes.

Antimicrobial Activity
Amoxicillin and clavulanic acid has been shown to be active against most isolates of the following microorganisms, both in vitro and in clinical infections [see Indications and Usage (1)] .

Gram-positive bacteria:
Staphylococcus aureus (methicillin-susceptible)
Streptococcus pneumoniae

Gram-negative bacteria:
Haemophilus influenzae
Haemophilus parainfluenzae
Klebsiella pneumoniae
Moraxella catarrhalis

The following in vitro data are available, but their clinical significance is unknown. At least 90 percent of the following bacteria exhibit in vitro minimum inhibitory concentration (MIC) less than or equal to the susceptible breakpoint for amoxicillin and clavulanic acid against isolates of similar genus or organism group. However, the efficacy of amoxicillin and clavulanic acid in treating clinical infections caused by these bacteria have not been established in adequate and well-controlled trials.

Gram-positive bacteria:
Streptococcus pyogenes

Susceptibility Testing:
For specific information regarding susceptibility test interpretive criteria and associated test methods and quality control standards recognized by FDA for this drug, please see https://www.fda.gov/STIC.

13 NONCLINICAL TOXICOLOGY

13.1 Carcinogenesis, Mutagenesis, Impairment of Fertility

Long-term studies in animals have not been performed to evaluate carcinogenic potential. Amoxicillin and clavulanate (4:1 ratio formulation of amoxicillin:clavulanate) was non-mutagenic in the Ames bacterial mutation assay, and the yeast gene conversion assay. Amoxicillin and clavulanate was weakly positive in the mouse lymphoma assay, but the trend toward increased mutation frequencies in this assay occurred at concentrations that were also associated with decreased cell survival. Amoxicillin and clavulanate was negative in the mouse micronucleus test, and in the dominant lethal assay in mice. Potassium clavulanate alone was tested in the Ames bacterial mutation assay and in the mouse micronucleus test and was negative in each of these assays.

Amoxicillin and clavulanate (2:1 ratio formulation of amoxicillin:clavulanate) at oral doses of up to 1,200 mg/kg/day was found to have no effect on fertility and reproductive performance in rats. Based on body surface area, this dose of amoxicillin is approximately 1.6 times the Maximum Human Recommended Dose (MHRD) in Amoxicillin and Clavulanate Potassium Extended Release Tablets and the clavulanate dose multiple is approximately 13 times higher than the MHRD.

14 CLINICAL STUDIES

14.1 Acute Bacterial Sinusitis

Adults with a diagnosis of acute bacterial sinusitis (ABS) were evaluated in 3 clinical studies. In one study, 363 patients were randomized to receive either Amoxicillin and Clavulanate Potassium Extended Release Tablets XR 2,000 mg/125 mg orally every 12 hours or levofloxacin 500 mg orally daily for 10 days in a double‑blind, multicenter, prospective trial. These patients were clinically and radiologically evaluated at the test of cure (day 17 to 28) visit. The combined clinical and radiological responses were 84% for Amoxicillin and Clavulanate Potassium Extended Release Tablets and 84% for levofloxacin at the test of cure visit in clinically evaluable patients (95% CI for the treatment difference equals ‑9.4, 8.3). The clinical response rates at the test of cure were 87% and 89%, respectively.

The other 2 trials were non‑comparative, multicenter studies designed to assess the bacteriological and clinical efficacy of Amoxicillin and Clavulanate Potassium Extended Release Tablets (2,000 mg/125 mg orally every 12 hours for 10 days) in the treatment of 2,288 patients with ABS. Evaluation timepoints were the same as in the prior study. Patients underwent maxillary sinus puncture for culture prior to receiving study medication. Patients with acute bacterial sinusitis due to S. pneumoniae with reduced susceptibility to penicillin were accrued through enrollment in these 2 open‑label non‑comparative clinical trials. Microbiologic eradication rates for key pathogens in these studies are shown in Table 4.

Table 4: Clinical Outcome for ABS
Penicillin MICs of S. pneumoniae; Isolates | Intent-To-Treat |  |  | Clinically Evaluable
Penicillin MICs of S. pneumoniae; Isolates | n/Na | % | 95% CIb | n/Na | % | 95% CIb
All S. pneumoniae | 344/370 | 93 | — | 318/326 | 98 | —
MIC greater than or equal to 2.0 mcg/mLc | 35/36 | 97 | 85.5, 99.9 | 30/31 | 96 | 83.3, 99.9
MIC equal to 2.0 mcg/mL | 23/24 | 96 | 78.9, 99.9 | 19/20 | 95 | 75.1, 99.9
MIC greater than or equal to 4.0 mcg/mLd | 12/12 | 100 | 73.5, 100 | 11/11 | 100 | 71.5, 100
H. influenzae | 265/305 | 87 | — | 242/259 | 93 | —
M. catarrhalis | 94/105 | 90 | — | 86/90 | 96 | —

a n/N equals patients with pathogen eradicated or presumed eradicated/total number of patients.
b Confidence limits calculated using exact probabilities.
c S. pneumoniae strains with penicillin MICs of greater than or equal to 2 mcg/mL are considered resistant to penicillin.
d Includes one patient each with S. pneumoniae penicillin MICs of 8 and 16 mcg/mL.

14.2 Community-Acquired Pneumonia

Four randomized, controlled, double‑blind clinical studies and one non‑comparative study were conducted in adults with community-acquired pneumonia (CAP). In comparative studies, 904 patients received Amoxicillin and Clavulanate Potassium Extended Release Tablets at a dose of 2,000 mg/125 mg orally every 12 hours for 7 or 10 days. In the non-comparative study to assess both clinical and bacteriological efficacy, 1,122 patients received Amoxicillin and Clavulanate Potassium Extended Release Tablets 2,000 mg/125 mg orally every 12 hours for 7 days. In the 4 comparative studies, the combined clinical success rate at test of cure ranged from 86% to 95% in clinically evaluable patients who received Amoxicillin and Clavulanate Potassium Extended Release Tablets.

Data on the efficacy of Amoxicillin and Clavulanate Potassium Extended Release Tablets in the treatment of community‑acquired pneumonia due to S. pneumoniae with reduced susceptibility to penicillin were accrued from the 4 controlled clinical studies and the 1 non‑comparative study. The majority of these cases were accrued from the non‑comparative study. Results are shown in Table 5.

Table 5: Clinical Outcome for CAP due to S. pneumoniae
Penicillin MICs of S. pneumoniae; Isolates | Intent-To-Treat |  |  | Clinically Evaluable
Penicillin MICs of S. pneumoniae; Isolates | n/Na | % | 95% CIb | n/Na | % | 95% CIb
All S. pneumoniae | 318/367 | 87 | — | 275/297 | 93 | —
MIC greater than or equal to 2.0 mcg/mLc | 30/35 | 86 | 69.7, 95.2 | 24/25 | 96 | 79.6, 99.9
MIC equal to 2.0 mcg/mL | 22/24 | 92 | 73.0, 99.9 | 18/18 | 100 | 81.5, 100
MIC greater than or equal to 4.0 mcg/mLd | 8/11 | 73 | 39.0, 94.0 | 6/7 | 86 | 42.1, 99.6

a.n/N equals patients with pathogen eradicated or presumed eradicated/total number of patients.
b.Confidence limits calculated using exact probabilities.
c. S. pneumoniae strains with penicillin MICs of greater than or equal to 2 mcg/mL are considered resistant to penicillin.
d.Includes one patient each with S. pneumoniae penicillin MICs of 8 and 16 mcg/mL in the Intent-To-Treat group only.

15 REFERENCES

1. Swanson-Biearman B, Dean BS, Lopez G, Krenzelok EP. The effects of penicillin and cephalosporin ingestions in children less than six years of age. Vet Hum Toxicol. 1988; 30:66-67.

16 HOW SUPPLIED/STORAGE AND HANDLING

How Supplied
Amoxicillin and Clavulanate Potassium Extended Release Tablets are white, oval film-coated bilayer scored tablets debossed with "AUGMENTIN XR". Each tablet contains 1,000 mg of amoxicillin (as amoxicillin sodium and amoxicillin trihydrate) and 62.5 mg clavulanic acid as the potassium salt.

Amoxicillin and Clavulanate Potassium Extended Release Tablets are supplied as follows:

- NDC 81964‑220‑28 Bottles of 28 (7-day XR pack)
- NDC 81964‑220‑40 Bottles of 40 (10-day XR pack)

Storage
Store tablets at or below 25°C (77°F). Dispense in original container.

17 PATIENT COUNSELING INFORMATION

Administration Instructions
Counsel patients to take Amoxicillin and Clavulanate Potassium Extended Release Tablets every 12 hours with a low fat meal or snack to reduce the possibility of gastrointestinal upset. If diarrhea develops and is severe or lasts more than 2 or 3 days, they should call their doctor [see Dosage and Administration (2.1), Warnings and Precautions (5.5)].

Allergic Reactions
Counsel patients that Amoxicillin and Clavulante Potassium Extended Release Tablets contains a penicillin class drug product that can cause allergic reactions in some individuals [see Warnings and Precautions (5.1, 5.3)].

Severe Cutaneous Adverse Reactions (SCAR)
Advise patients about the signs and symptoms of serious skin manifestations. Instruct patients to stop taking Amoxicillin and Clavulanate Potassium Extended Release Tablets immediately and promptly report the first signs or symptoms of skin rash, mucosal lesions, or any other sign of hypersensitivity [see Warnings and Precautions (5.2)].

Diarrhea
Counsel patients that diarrhea is a common problem caused by antibacterial drugs, including Amoxicillin and Clavulanate Potassium Extended Release Tablets, which usually ends when the antibacterial is discontinued. Sometimes after starting treatment with antibacterial drugs, patients can develop watery and bloody stools (with or without stomach cramps and fever) even as late as 2 or more months after having taken the last dose of the antibacterial drug. If diarrhea is severe or lasts more than 2 or 3 days, patients should contact their physician as soon as possible [see Warnings and Precautions (5.5)].

Antibacterial Resistance
Patients should be counseled that antibacterial drugs, including Amoxicillin and Clavulanate Potassium Extended Release Tablets, should only be used to treat bacterial infections. Antibacterial drugs do not treat viral infections (e.g., the common cold). When Amoxicillin and Clavulanate Potassium Extended Release Tablets is prescribed to treat a bacterial infection, patients should be told that although it is common to feel better early in the course of therapy, the medication should be taken exactly as directed. Skipping doses or not completing the full course of therapy may: (1) decrease the effectiveness of the immediate treatment, and (2) increase the likelihood that bacteria will develop resistance and will not be treatable by Amoxicillin and Clavulanate Potassium Extended Release Tablets or other antibacterial drugs in the future [see Warnings and Precautions (5.8)].

Manufactured by:
USAntibiotics, LLC
Bristol, TN 37620 (USA)

MAALOX is a registered trademark of Novartis Consumer Health, Inc.

CLINITEST is a registered trademark of Miles, Inc.

Bottle Label (28s) Extended Release Tablets

NDC 81964- 220-28
1000 mg/62.5 mg

7 day XR pack

AMOXICILLIN AND

CLAVULANATE

POTASSIUM
extended-release tablets, USP

AMOXICILLIN, 1000 mg
(437.5 mg as amoxicillin sodium and

562.5 mg as amoxicillin trihydrate), and
CLAVULANIC ACID, 62.5 mg
(equivalent to 74.5 mg of clavulanate

potassium)

28 Scored Tablets

U

S

ANTIBIOTICS Rx only

Bottle Label (40s) Extended Release Tablets

NDC 81964- 220-40
1000 mg/62.5 mg

10 day XR pack

AMOXICILLIN AND

CLAVULANATE

POTASSIUM
extended-release tablets, USP

AMOXICILLIN, 1000 mg
(437.5 mg as amoxicillin sodium and

562.5 mg as amoxicillin trihydrate), and
CLAVULANIC ACID, 62.5 mg
(equivalent to 74.5 mg of clavulanate

potassium)

40 Scored Tablets

U

S

ANTIBIOTICS Rx only